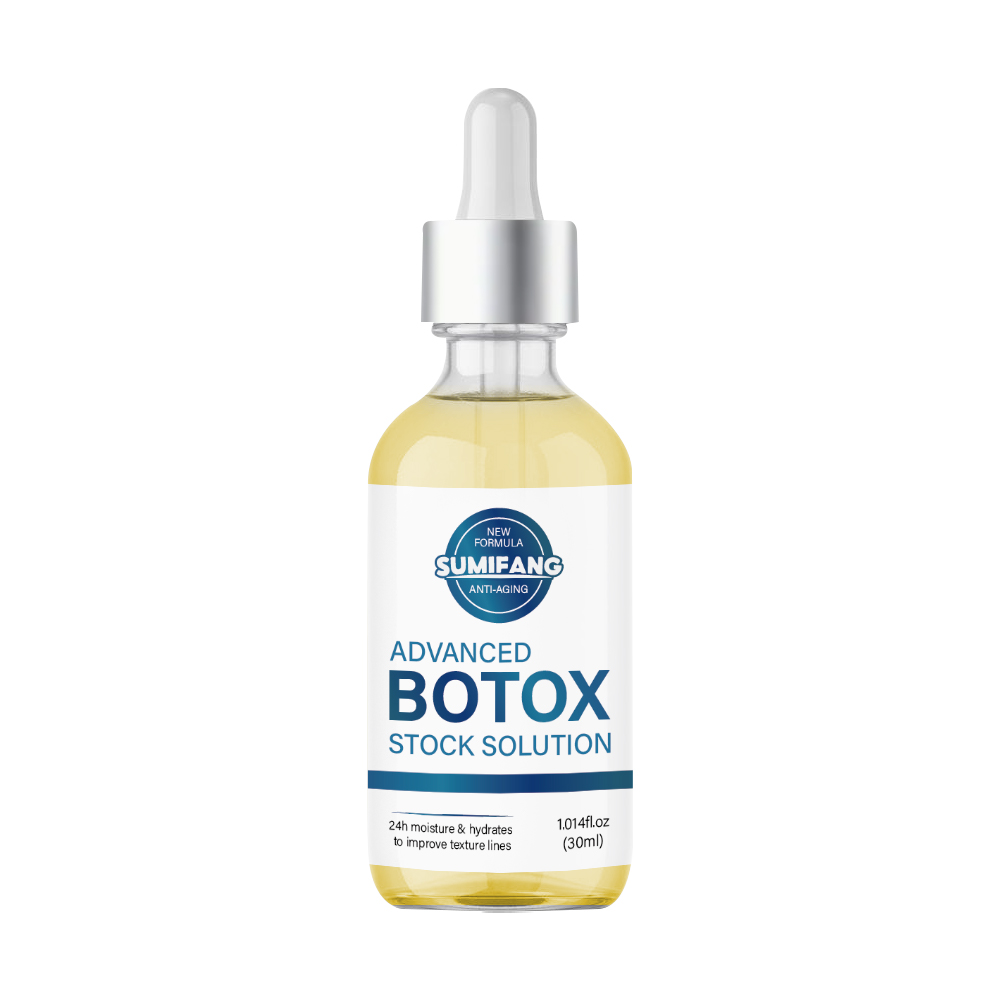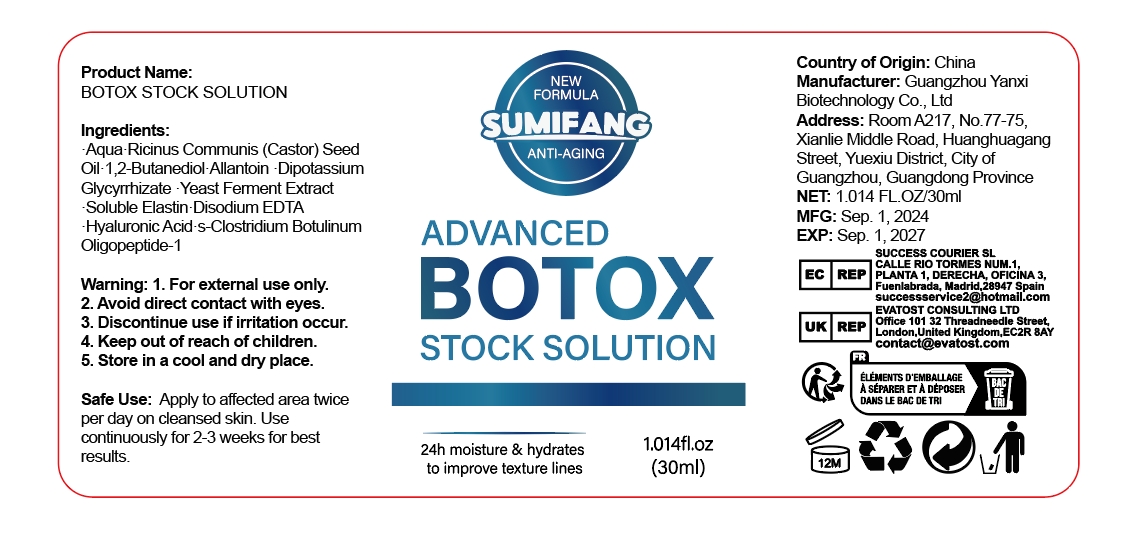 DRUG LABEL: Facial essence
NDC: 84025-199 | Form: OIL
Manufacturer: Guangzhou Yanxi Biotechnology Co., Ltd
Category: otc | Type: HUMAN OTC DRUG LABEL
Date: 20241008

ACTIVE INGREDIENTS: NIACINAMIDE 5 mg/100 mL; CETEARYL OLIVATE 3 mg/100 mL
INACTIVE INGREDIENTS: WATER

DOSAGE AND ADMINISTRATION

USE AS FACE

WARNINGS

keep out of children

INACTIVE INGREDIENT

Aqua

INDICATIONS AND USAGE

for face care

keep out of children

PURPOSE

For moisturizing the face